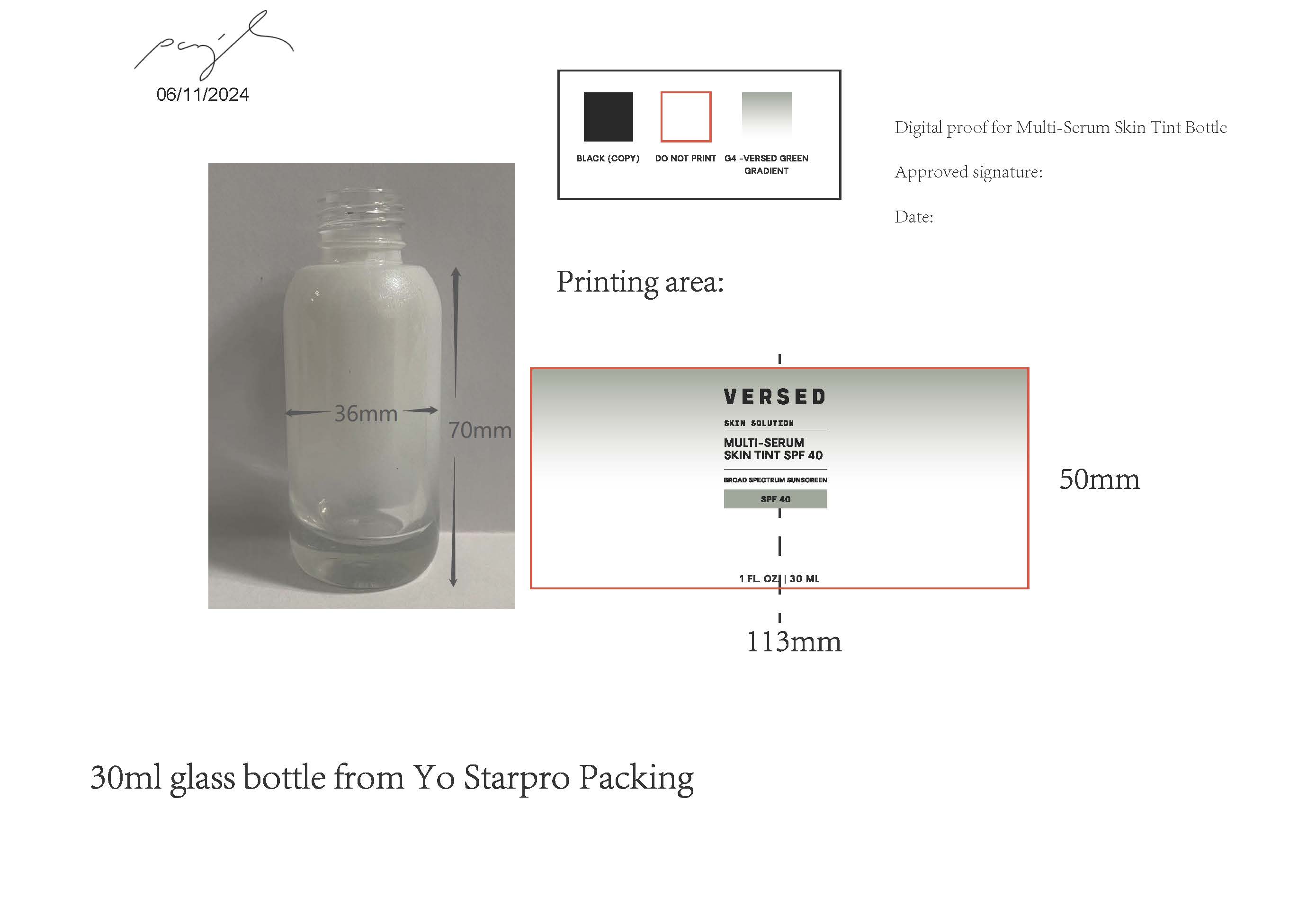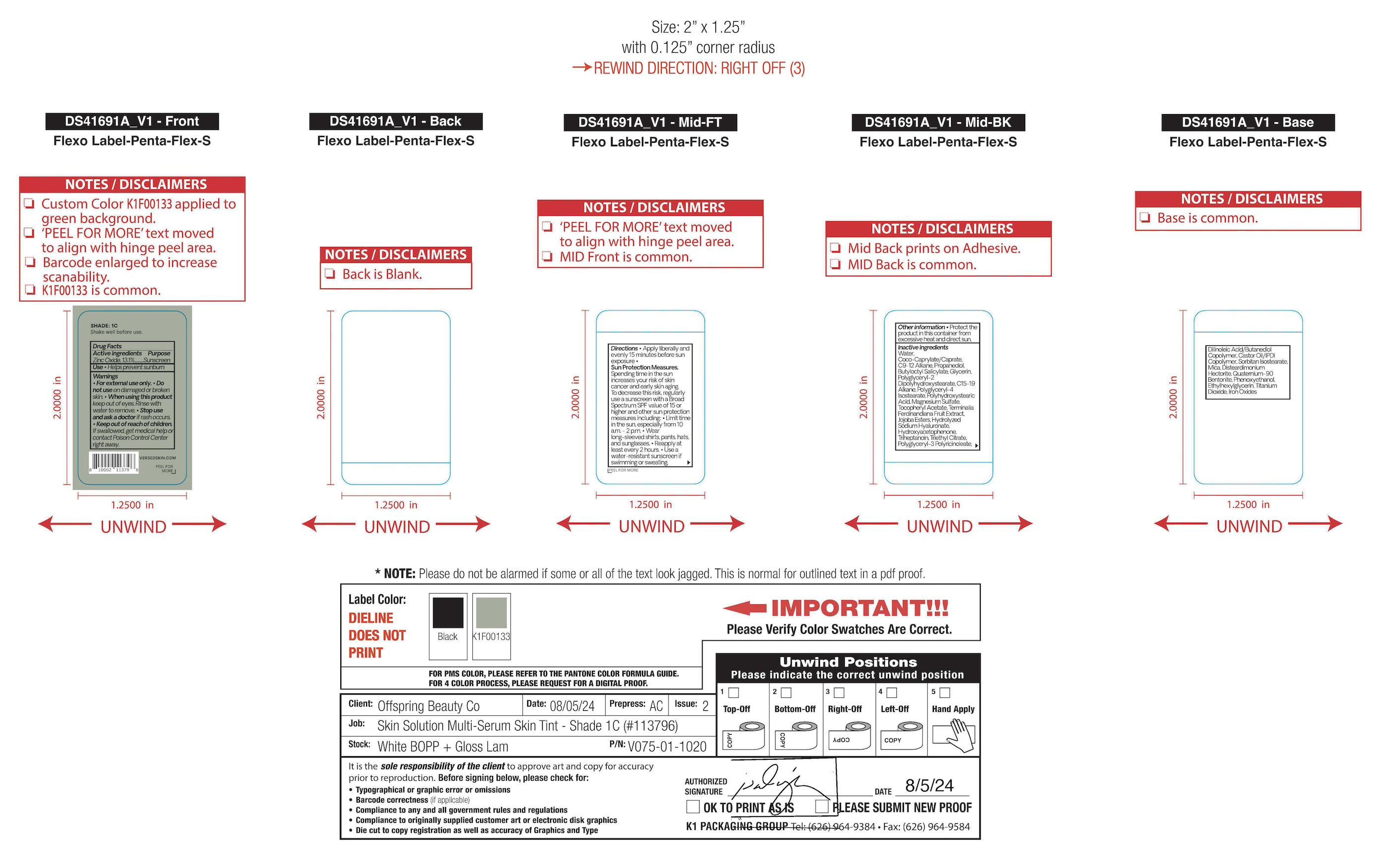 DRUG LABEL: Skin Solution Multi-Serum Skin Tint
NDC: 73690-030 | Form: LIQUID
Manufacturer: Offspring Beauty Co.
Category: otc | Type: HUMAN OTC DRUG LABEL
Date: 20251023

ACTIVE INGREDIENTS: ZINC OXIDE 13.1 g/100 mL
INACTIVE INGREDIENTS: CI 77499; KAKADU PLUM; TRIETHYL CITRATE; PROPANEDIOL; POLYGLYCERYL-3 PENTARICINOLEATE; CASTOR OIL/IPDI COPOLYMER; POLYGLYCERYL-2 DIPOLYHYDROXYSTEARATE; SORBITAN ISOSTEARATE; ETHYLHEXYLGLYCERIN; COCO-CAPRYLATE/CAPRATE; TITANIUM DIOXIDE; POLYHYDROXYSTEARIC ACID (2300 MW); TRIHEPTANOIN; PHENOXYETHANOL; CI 77491; DISTEARDIMONIUM HECTORITE; C15-19 ALKANE; MAGNESIUM SULFATE, UNSPECIFIED; .ALPHA.-TOCOPHEROL ACETATE; WATER; JOJOBA OIL, RANDOMIZED; SODIUM HYALURONATE; MICA; DILINOLEIC ACID/BUTANEDIOL COPOLYMER; QUATERNIUM-90 BENTONITE; HYDROXYACETOPHENONE; C9-12 ALKANE; BUTYLOCTYL SALICYLATE; GLYCERIN; POLYGLYCERYL-4 ISOSTEARATE; CI 77492

Versed - Skin Solution Multi-Serum Skin Tint SPF 40

ACTIVE INGREDIENTS

Zinc Oxide 13.1%

PURPOSE

SUNSCREEN

USE

- HELPS PREVENT SUNBURN

WARNINGS

- FOR EXTERNAL USE ONLY.
- DO NOT USE ON DAMAGE OR BROKEN SKIN.
- WHEN USING THIS PRODUCT KEEP OUT OF EYES. RINSE WITH WATER TO REMOVE.

- KEEP OUT OF REACH OF CHILDREN. IF SWALLOWED, GET MEDICAL HELP OR CONTACT POISON CONTROL CENTER RIGHT AWAY.

- STOP USE AND ASK A DOCTOR IF RASH OCCURS.

DIRECTIONS

- APPLY LIBERALLY AND EVENLY 15 MINUTES BEFORE SUN EXPOSURE.
- REAPPLY AT LEAST EVERY 2 HOURS
- USE A WATER-RESISTANT SUNSCREEN IF SWIMMING OR SWEATING

OTHER SAFETY INFORMATION

SUN PROTECTION MEASURES: SPENDING TIME IN THE SUN INCREASES YOUR RISK OF SKIN CANCER AND EARLY SKIN AGING. TO DECREASE THIS RISK, REGULARLY USE A SUNSCREEN WITH A BROAD SPECTRUM SPF VALUE OF 15 OR HIGHER AND OTHER SUN PROTECTION MEASURES INCLUDING:

- LIMIT TIME IN THE SUN, ESPECIALLY FROM 10 A.M. - 2 P.M.
- WEAR LONG-SLEEVED SHIRTS, PANTS, HATS, AND SUNGLASSES

OTHER INFORMATION

- PROTECT THE PRODUCT IN THIS CONTAINER FROM EXCESSIVE HEAT AND DIRECT SUN.

INACTIVE INGREDIENTS

Water, Coco-Caprylate/Caprate, C9-12 Alkane, Propanediol, Butyloctyl Salicylate, Glycerin, Polyglyceryl-2 Dipolyhydroxystearate, C15-19 Alkane, Polyglyceryl-4 Isostearate, Polyhydroxystearic Acid, Magnesium Sulfate, Tocopheryl Acetate, Terminalia Ferdinandiana Fruit Extract, Jojoba Esters, Hydrolyzed Sodium Hyaluronate, Hydroxyacetophenone, Triheptanoin, Triethyl Citrate, Polyglyceryl-3 Polyricinoleate, Dilinoleic Acid/Butanediol Copolymer, Castor Oil/IPDI Copolymer, Sorbitan Isostearate, Mica, Disteardimonium Hectorite, Quaternium-90 Bentonite, Phenoxyethanol, Ethylhexylglycerin, Titanium Dioxide, Iron Oxides